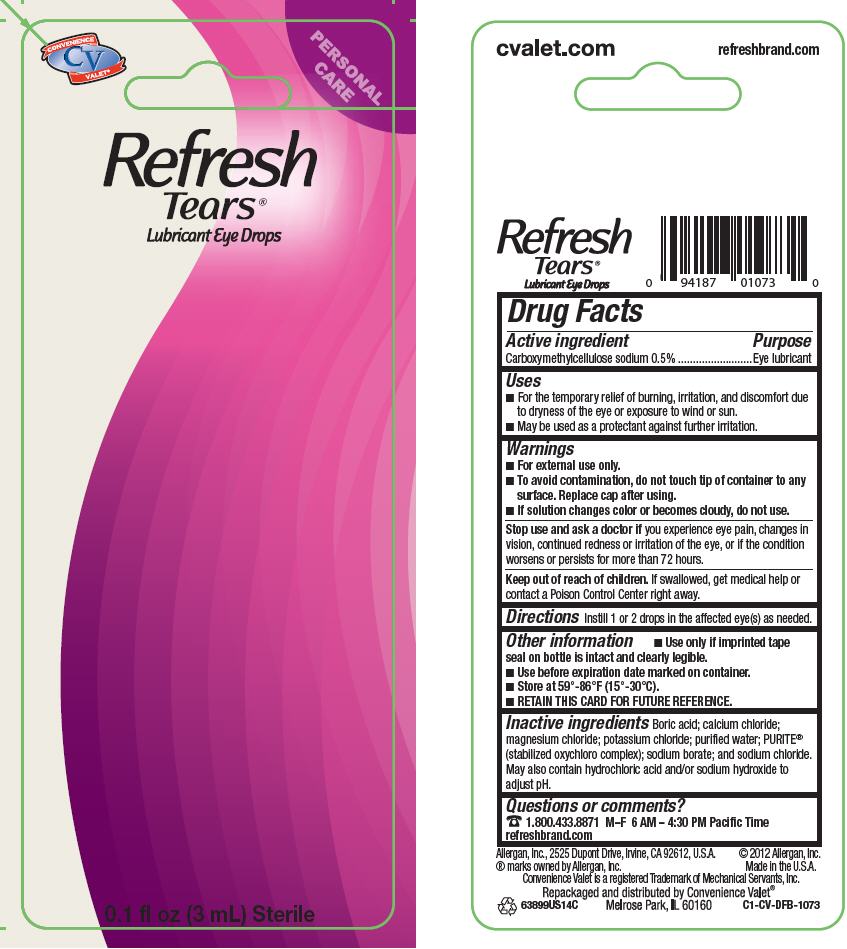 DRUG LABEL: REFRESH TEARS
NDC: 29485-1073 | Form: SOLUTION/ DROPS
Manufacturer: Mechanical Servants, Inc.
Category: otc | Type: HUMAN OTC DRUG LABEL
Date: 20121108

ACTIVE INGREDIENTS: carboxymethylcellulose sodium 5 mg/1 mL
INACTIVE INGREDIENTS: boric acid; calcium chloride; magnesium chloride; potassium chloride; water; sodium chlorite; sodium chlorate; chlorine dioxide; sodium borate; sodium chloride; hydrochloric acid; sodium hydroxide

REFRESH TEARS®

Drug Facts

Active ingredient

Carboxymethylcellulose sodium 0.5%

Purpose

Eye lubricant

Uses

- For the temporary relief of burning, irritation, and discomfort due to dryness of the eye or exposure to wind or sun.
- May be used as a protectant against further irritation.

Warnings

- For external use only.
- To avoid contamination, do not touch tip of container to any surface. Replace cap after using.
- If solution changes color or becomes cloudy, do not use.

Stop use and ask a doctor if you experience eye pain, changes in vision, continued redness or irritation of the eye, or if the condition worsens or persists for more than 72 hours.

Keep out of reach of children. If swallowed, get medical help or contact a Poison Control Center right away.

Directions

Instill 1 or 2 drops in the affected eye(s) as needed.

Other information

- Use only if imprinted tape seal on bottle is intact and clearly legible.
- Use before expiration date marked on container.
- Store at 59°-86°F (15°-30°C).
- RETAIN THIS CARD FOR FUTURE REFERENCE.

Inactive ingredients

Boric acid; calcium chloride; magnesium chloride; potassium chloride; purified water; PURITE® (stabilized oxychloro complex); sodium borate; and sodium chloride. May also contain hydrochloric acid and/or sodium hydroxide to adjust pH.

Questions or comments?

1.800.433.8871 M–F 6 AM – 4:30 PM Pacific Time
refreshbrand.com

Repackaged and distributed by Convenience Valet®
Melrose Park, IL 60160

PRINCIPAL DISPLAY PANEL - 3 mL Bottle Label

CONVENIENCE
CV
VALET®

PERSONAL
CARE

Refresh
Tears®
Lubricant Eye Drops

0.1 fl oz (3 mL) Sterile